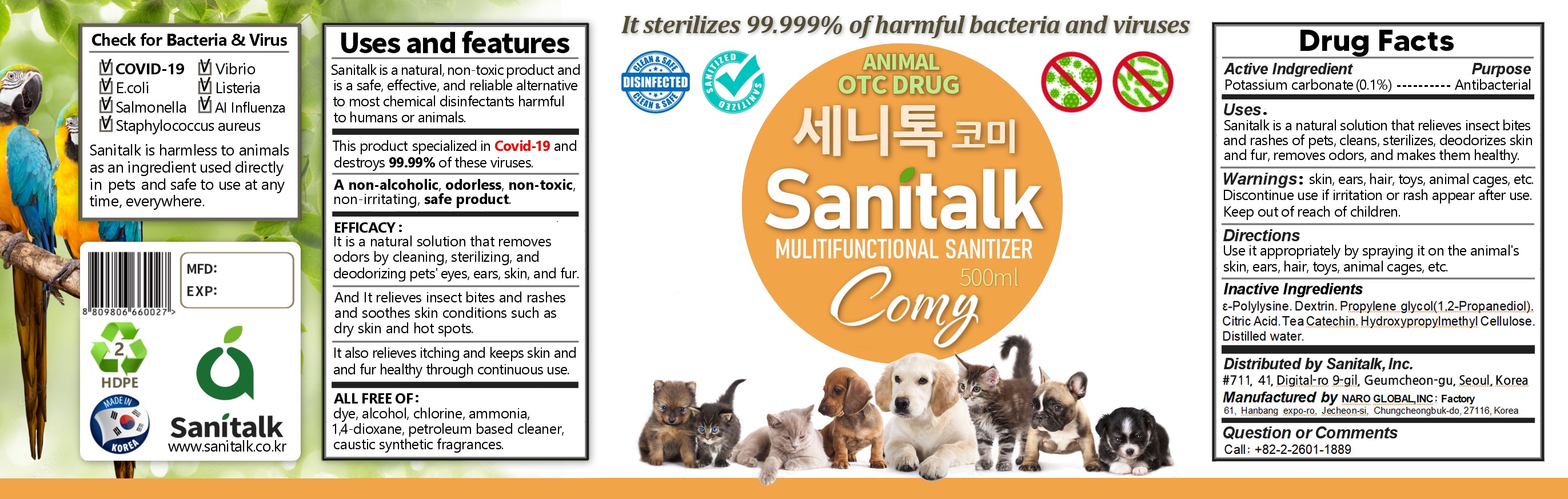 DRUG LABEL: SANITALK COMY - ANIMAL SANITIZER(COVID-19)
NDC: 82486-0004 | Form: LIQUID
Manufacturer: Sanitalk Inc
Category: animal | Type: OTC ANIMAL DRUG LABEL
Date: 20180117

ACTIVE INGREDIENTS: POTASSIUM CARBONATE 0.1 g/100 mL
INACTIVE INGREDIENTS: WATER

ACTIVE INGREDIENT

Potassium carbonate

INACTIVE INGREDIENT

Water, Citric Acid, .ε-Polylysine, Dextrin, 1,2-Propanediol, Tea Catechin, Hydroxypropylmethyl Cellulose

PURPOSE

Antibacterial

Keep out of reach of children

INDICATIONS AND USAGE

Use it appropriately by spraying it on the animal's skin, ears, hair, toys, animal cages, etc.

WARNINGS

Skin, ears, hair, toys, animal cages, etc.

Discontinue use if irritation or rash appear after use.

Keep out of reach of children.

DOSAGE AND ADMINISTRATION

For external use only